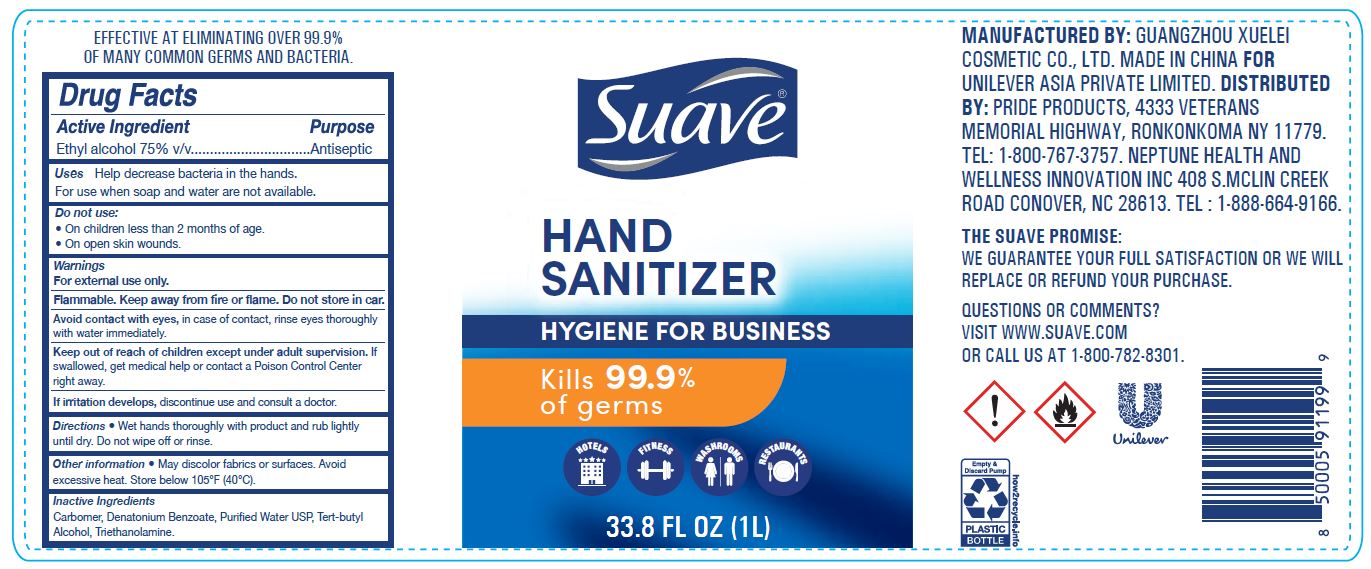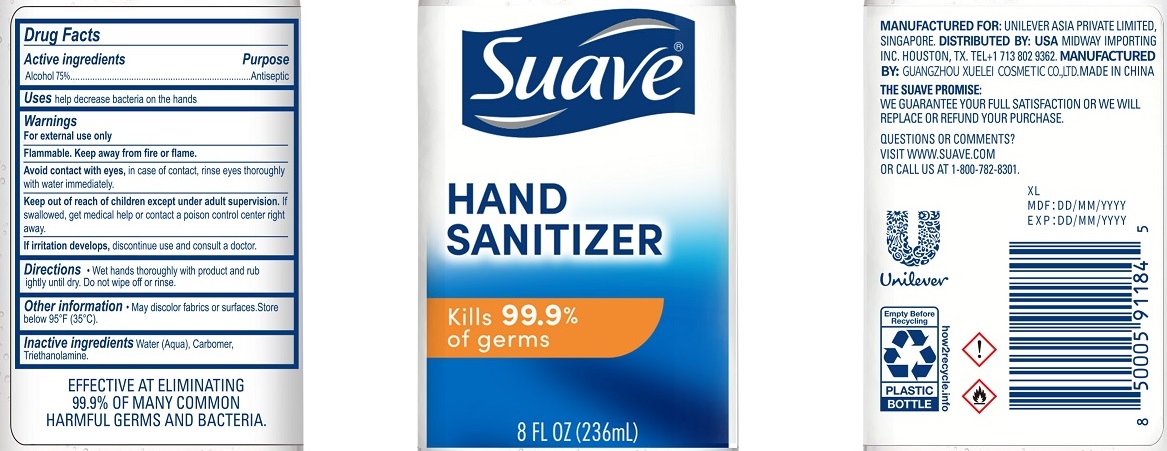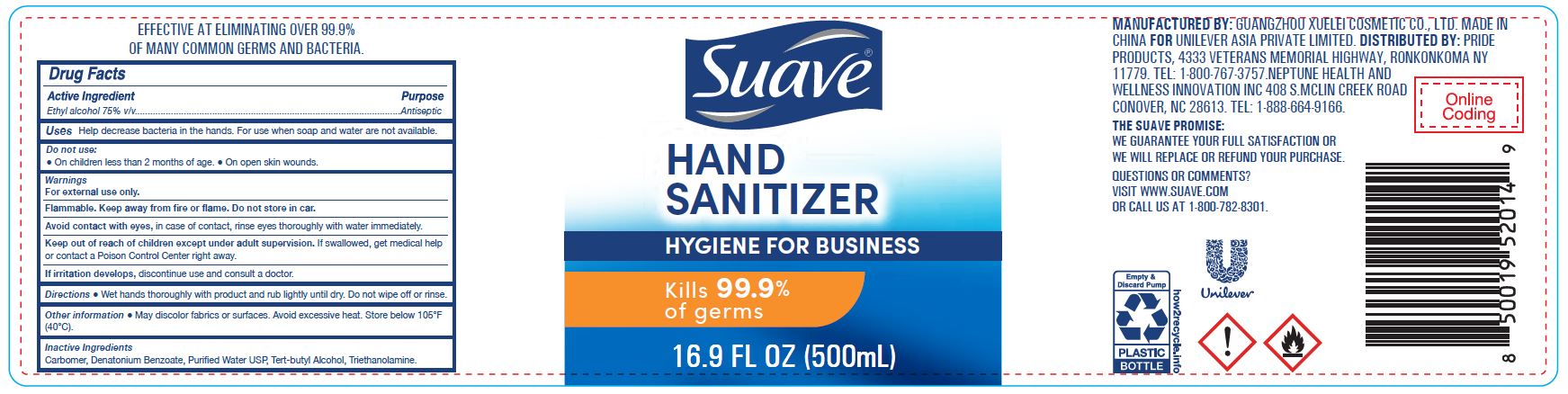 DRUG LABEL: Suave Hand Sanitizer Professional
NDC: 50069-109 | Form: GEL
Manufacturer: UNILEVER ASIA PRIVATE LIMITED
Category: otc | Type: HUMAN OTC DRUG LABEL
Date: 20201123

ACTIVE INGREDIENTS: ALCOHOL 75 mL/100 mL
INACTIVE INGREDIENTS: CARBOMER HOMOPOLYMER, UNSPECIFIED TYPE; DENATONIUM BENZOATE; WATER; TERT-BUTYL ALCOHOL; TROLAMINE

Suave Hand Sanitizer Professional - 75% Ethyl Alcohol

ACTIVE INGREDIENT

Alcohol (75% v/v)

PURPOSE

ANTISEPTIC

USE

Help decrease bacteria on the hands. For use when soap and water are not available.

WARNINGS

For external use only.

Flammable. Keep away from fire or flame. Do not store in car.

Avoid contact with eyes, in case of contact, rinse eyes thoroughly with water immediately.

If irritation develops, discontinue use and consult a doctor.

Keep out of reach of children.

If swallowed, get medical help or contact a Poison Control Center right away.

Do not use:

- On children less than 2 months of age.
- On open skin wounds.

Keep out of reach of children except under adult supervision. If swallowed, get medical help or contact a poison control center right away.

DIRECTIONS

- Wet hands thoroughly with product and rub lightly until dry. Do not wipe off or rinse.

OTHER INFORMATION

- May discolor fabrics or surfaces. Store below 95°F (35°C).

INACTIVE INGREDIENTS

Carbomer, Denatonium Benzoate, Purified Water USP, Tert-butyl Alcohol, Triethanolamine.